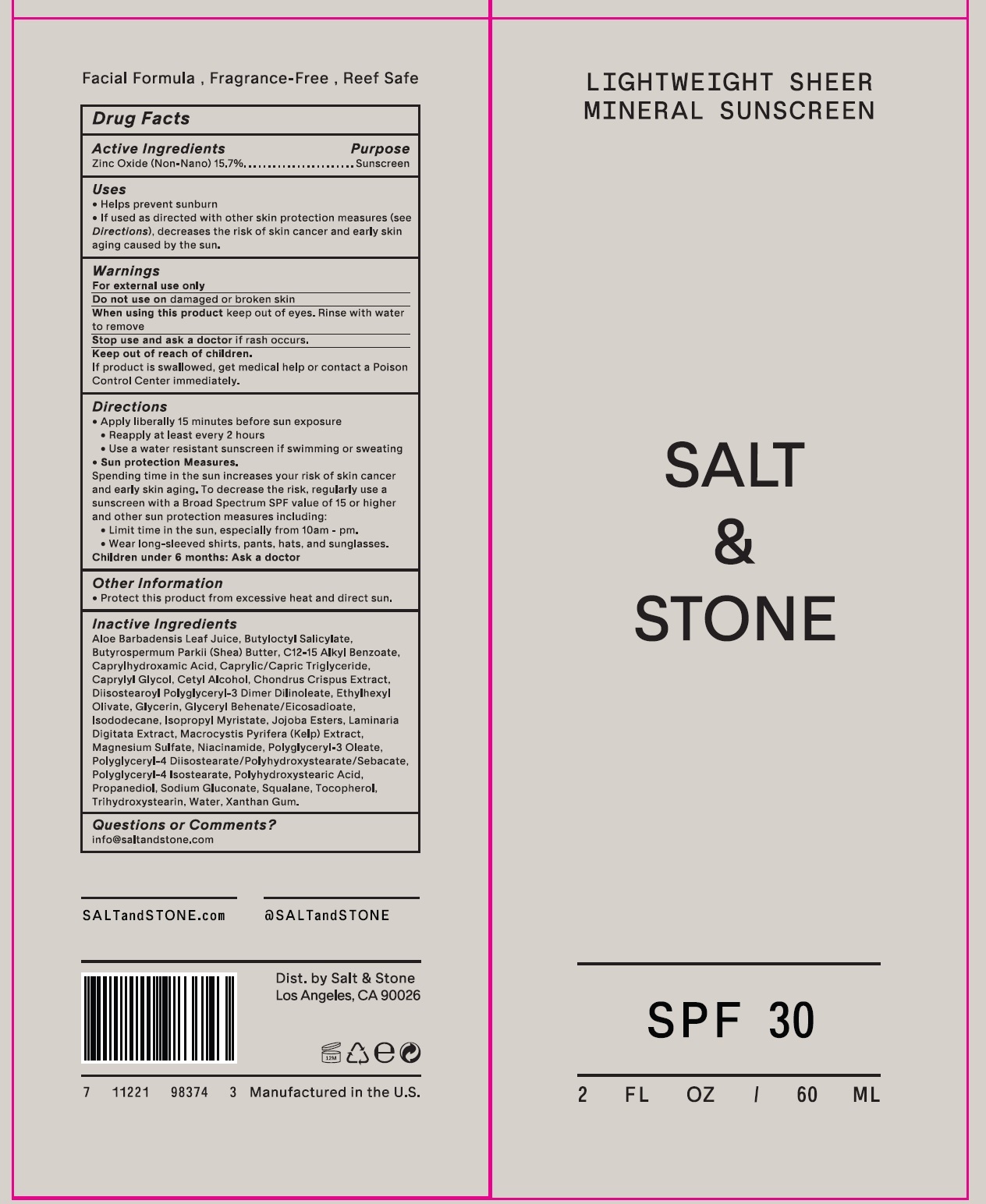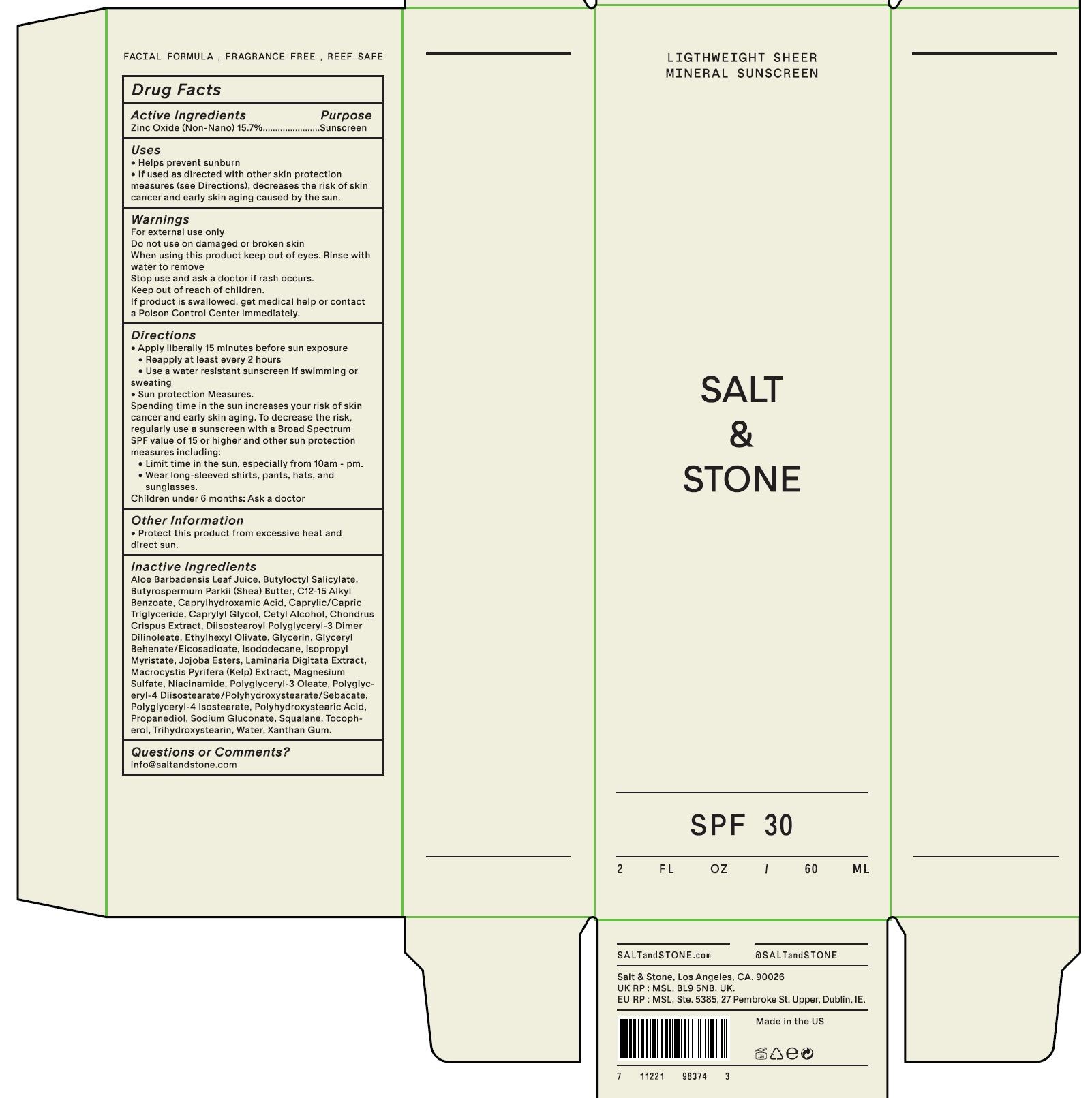 DRUG LABEL: Salt and Stone Lightweight Sheer Mineral Sunscreen SPF30
NDC: 71585-144 | Form: LOTION
Manufacturer: SALT & STONE, INC.
Category: otc | Type: HUMAN OTC DRUG LABEL
Date: 20231028

ACTIVE INGREDIENTS: ZINC OXIDE 157 mg/1 mL
INACTIVE INGREDIENTS: ALOE VERA LEAF; BUTYLOCTYL SALICYLATE; SHEA BUTTER; ALKYL (C12-15) BENZOATE; CAPRYLHYDROXAMIC ACID; MEDIUM-CHAIN TRIGLYCERIDES; CAPRYLYL GLYCOL; CETYL ALCOHOL; CHONDRUS CRISPUS CARRAGEENAN; DIISOSTEAROYL POLYGLYCERYL-3 DIMER DILINOLEATE; GLYCERIN; GLYCERYL BEHENATE/EICOSADIOATE; ISODODECANE; ISOPROPYL MYRISTATE; LAMINARIA DIGITATA; MACROCYSTIS PYRIFERA; MAGNESIUM SULFATE, UNSPECIFIED FORM; NIACINAMIDE; POLYGLYCERYL-3 OLEATE; POLYGLYCERYL-4 DIISOSTEARATE/POLYHYDROXYSTEARATE/SEBACATE; PROPANEDIOL; SODIUM GLUCONATE; SQUALANE; TOCOPHEROL; TRIHYDROXYSTEARIN; WATER; XANTHAN GUM

Salt & Stone Lightweight Sheer Mineral Sunscreen SPF30

Active Ingredients

Zinc Oxide (Non-Nano) 15.7%

Purpose

Sunscreen

Uses

- Helps prevent sunburn
- If used as directed with other skin protection measures (see Directions), decreases the risk of skin cancer and early skin aging caused by the sun.

Warnings

For external use only

Do not use

on damaged or broken skin

When using this product

keep out of eyes. Rinse with water to remove

Stop use and ask a doctor

if rash occurs.

Keep out of reach of children.

If product is swallowed, get medical help or contact a Poison Control Center immediately.

Directions

- Apply liberally 15 minutes before sun exposure
- Reapply at least every 2 hours
- Use a water resistant sunscreen if swimming or sweating
- Sun protection Measures.

- Limit time in the sun, especially from 10am - pm.
- Wear long-sleeved shirts, pants, hats, and sunglasses.

Spending time in the sun increases your risk of skin cancer and early skin aging. To decrease the risk, regularly use a sunscreen with a Broad Spectrum SPF value of 15 or higher and other sun protection measures including:

Children under 6 months: Ask a doctor

Other Information

- Protect this product from excessive heat and direct sun.

Inactive Ingredients

Aloe Barbadensis Leaf Juice, Butyloctyl Salicylate, Butyrospermum Parkii (Shea) Butter, C12-15 Alkyl Benzoate, Caprylhydroxamic Acid, Caprylic/Capric Triglyceride, Caprylyl Glycol, Cetyl Alcohol, Chondrus Crispus Extract, Diisostearoyl Polyglyceryl-3 Dimer Dilinoleate, Ethylhexyl Olivate, Glycerin, Glyceryl Behenate/Eicosadioate, Isododecane, Isopropyl Myristate, Jojoba Esters, Laminaria Digitata Extract, Macrocystis Pyrifera (Keip) Extract, Magnesium Sulfate, Niacinamide, Polyglyceryl-3 Oleate, Polyglyceryl-4 Diisostearate/Polyhydroxystearate/Sebacate, Polyglyceryl-4 Diisostearate, Polyhydroxystearic Acid, Propanediol, Sodium Gluconate, Squalane, Tocopherol, Trihydroxystearin, Water, Xanthan Gum.

Questions or Comments?

info@saltandstone.com